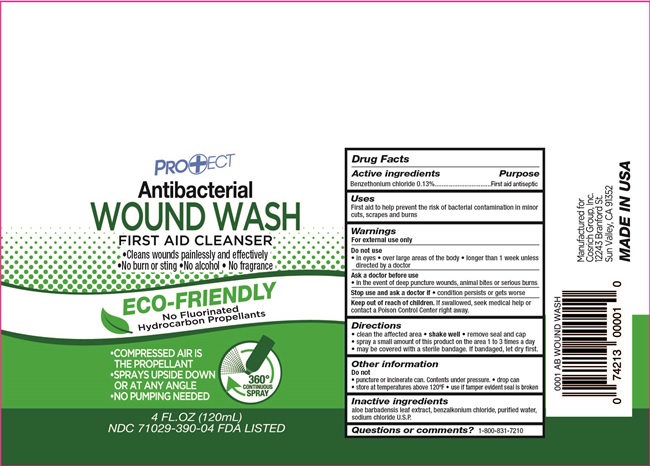 DRUG LABEL: Sterile Antibacterial Wound Wash
NDC: 71029-390 | Form: SPRAY
Manufacturer: Cosrich Group, Inc.
Category: otc | Type: HUMAN OTC DRUG LABEL
Date: 20251118

ACTIVE INGREDIENTS: BENZETHONIUM CHLORIDE 1.3 mg/1 mL
INACTIVE INGREDIENTS: ALOE VERA LEAF; WATER; SODIUM CHLORIDE; BENZALKONIUM CHLORIDE

Drug Facts

Active ingredients

Benzethonium Chloride 0.13%

Purpose

First Aid Antiseptic

Uses

first aid to help prevent the risk of bacterial contamination in minor cuts, scrapes and burns.

Warnings

For external use only

Do not use

- in eyes
- over large areas of the body
- longer than 1 week unless directed by a doctor

Ask a doctor before use

in the event of deep puncture wounds, animal bites or severe burns

Stop use and ask a doctor if

- condition persists or gets worse

Keep out of reach of childrens

If swallowed get medical help or contact a Poison Control Center right away

Directions

- clean the affected area
- shake well
- remove seal and cap
- spray a small amount of this product on the area 1 to 3 times a day
- may be covered with a sterile bandage. If bandaged, let dry first

Other information

Do not

- puncture or incinerate can. Contents under pressure
- drop can
- store at temperatures above 120oF.
- use if tamper evident seal is broken

Inactive ingredients

Aloe Barbadensis Leaf Extract, benzalkonium chloride, Purified Water, Sodium Chloride U.S.P.

Questions?

1-800-831-7210

Principal Display Panel

NDC 71029-390-04

PRO+ECT

Antibacterial WOUND WASH

FIRST AID CLEANSER

- Cleans wounds painlessly and effectively
- No burn or sting
- No alcohol
- No fragrance

ECO-FRIENDLY

No Fluorinated Hydrocarbon Propellants

- COMPRESSED AIR IS THE PROPELLANT
- SPRAYS UPSIDE DOWN OR AT ANY ANGLE
- NO PUMPING NEEDED

360^0 CONTINUOUS SPRAY

4 FL.OZ (120 mL)